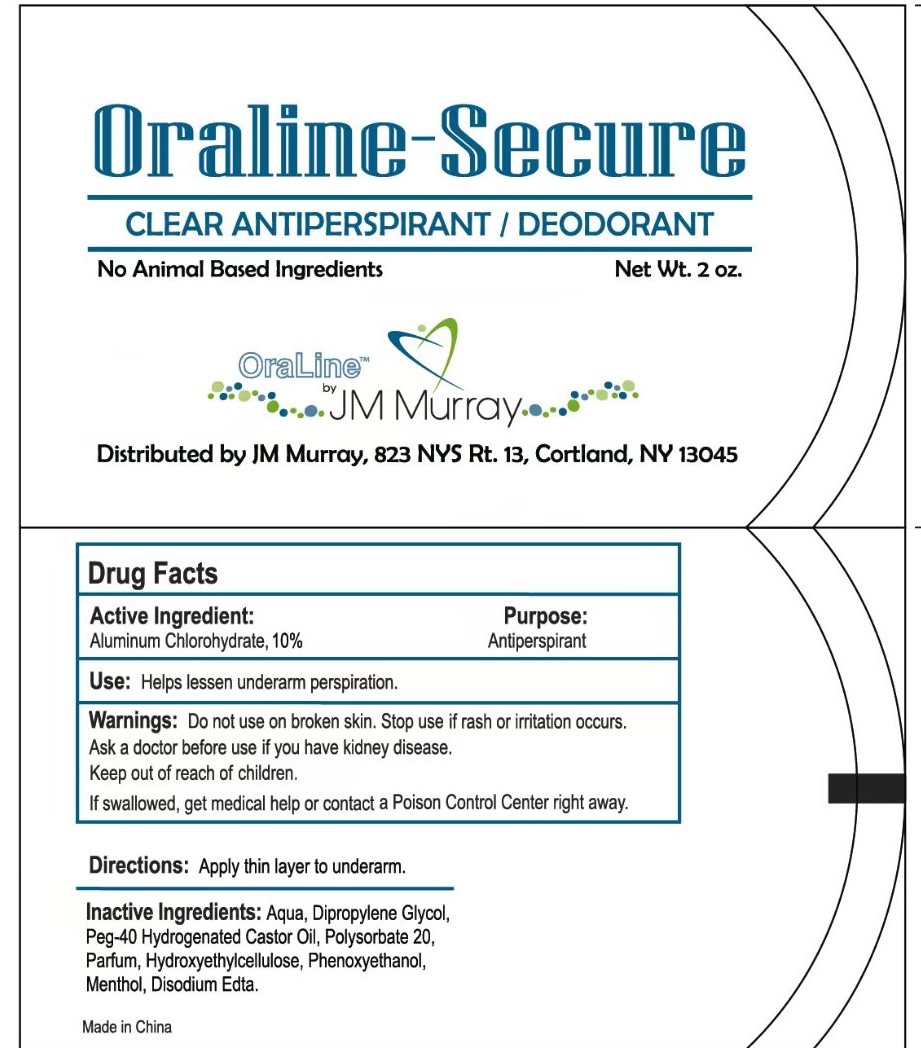 DRUG LABEL: ORALINE-SECURE ANTIPERSPIRANT 2 OZ
NDC: 84641-005 | Form: LIQUID
Manufacturer: NANTONG QINJI HEALTH TECHNOLOGY CO., LTD.
Category: otc | Type: HUMAN OTC DRUG LABEL
Date: 20250116

ACTIVE INGREDIENTS: ALUMINUM CHLOROHYDRATE 1 g/10 g
INACTIVE INGREDIENTS: AQUA; DIPROPYLENE GLYCOL; POLYSORBATE 20; HYDROXYETHYLCELLULOSE; PHENOXYETHANOL; EDETATE DISODIUM; PEG-40 HYDROGENATED CASTOR OIL; MENTHOL

84641-005

Active ingredients

ALUMINUM CHLOROHYDRATE 10% w/w

Purpose

Antiperspirant

Use

Helps lessen underarm perspiration.

Warnings

For external use only.

Do not use

on broken skin.

Stop use if

rash or irritation occurs.

Ask a doctor before use if

you have kidney disease.

Keep out of children.

If swallowed, get medical help or contact a Poison Control Center right away.

Directions

Apply thin layer to underam.

Inactive ingredients

Aqua,dipropylene Glycol,peg-40 Hydrogenated Castor Oil, Polysorbate 20, Parfum, Hydroxyethylcellulose, Phenoxyethanol, Menthol, Disodium EDTA